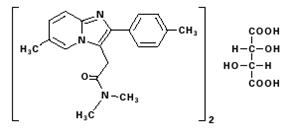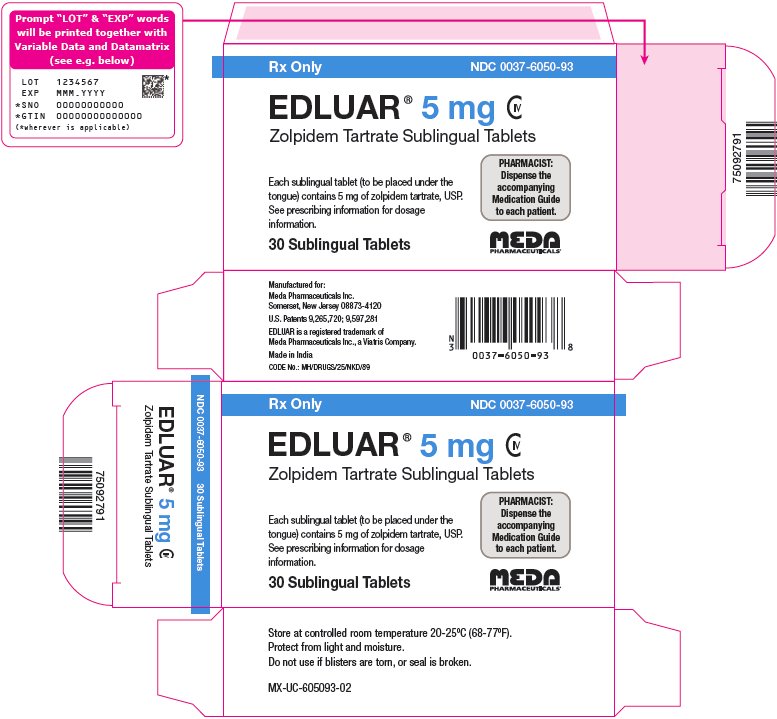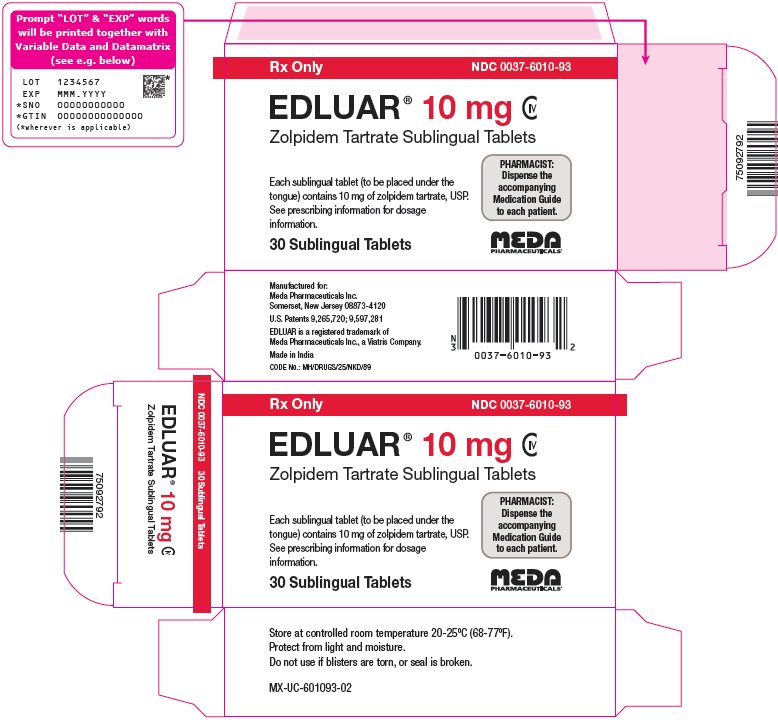 DRUG LABEL: Edluar
NDC: 0037-6050 | Form: TABLET
Manufacturer: Viatris Specialty LLC
Category: prescription | Type: HUMAN PRESCRIPTION DRUG LABEL
Date: 20220815
DEA Schedule: CIV

ACTIVE INGREDIENTS: ZOLPIDEM TARTRATE 5 mg/1 1
INACTIVE INGREDIENTS: MANNITOL; SILICON DIOXIDE; MICROCRYSTALLINE CELLULOSE; CROSCARMELLOSE SODIUM; SACCHARIN SODIUM; MAGNESIUM STEARATE

HIGHLIGHTS OF PRESCRIBING INFORMATION

These highlights do not include all the information needed to use EDLUAR safely and effectively. See full prescribing information for EDLUAR.
EDLUAR® (zolpidem tartrate) sublingual tablets, for oral use, CIV
Initial U.S. Approval: 1992

RECENT MAJOR CHANGES

Boxed Warning 08/2019
Contraindications (4) 08/2019
Warnings and Precautions, Complex Sleep Behaviors (5.1) 08/2019
Warnings and Precautions, CNS Depressant Effects and Next-Day Impairment (5.2) 12/2018

WARNING: COMPLEX SLEEP BEHAVIORS

See full prescribing information for complete boxed warning.

Complex sleep behaviors including sleep-walking, sleep-driving, and engaging in other activities while not fully awake may occur following use of Edluar. Some of these events may result in serious injuries, including death. Discontinue Edluar immediately if a patient experiences a complex sleep behavior. (4, 5.1)

1 INDICATIONS AND USAGE

Edluar, a gamma-aminobutyric acid (GABA) A receptor positive modulator, is indicated for the short-term treatment of insomnia characterized by difficulties with sleep initiation. Zolpidem tartrate has been shown to decrease sleep latency for up to 35 days in controlled clinical studies. (1)

2 DOSAGE AND ADMINISTRATION

- Use the lowest dose effective for the patient (2.1)
- Recommended dose is 5 mg for women and 5 or 10 mg for men, immediately before bedtime. (2.1)
- Geriatric patients and patients with hepatic impairment: Recommended dose is 5 mg for men and women. (2.2)
- Lower doses of CNS depressants may be necessary when taken concomitantly with Edluar. (2.3)
- Co-administration with CNS depressants: Recommended dose is 5 mg for men and women. (2.3)
- The effect of Edluar may be slowed if taken with or immediately after a meal. (2.4)
- Edluar sublingual tablet should be placed under the tongue, where it will disintegrate. (2.4)
- The tablet should not be swallowed and the tablet should not be taken with water. (2.4)

3 DOSAGE FORMS AND STRENGTHS

Sublingual tablets: 5 mg and 10 mg. Tablets not scored. (3)

4 CONTRAINDICATIONS

- Patients who have experienced complex sleep behaviors after taking Edluar. (4, 5.1)
- Known hypersensitivity to zolpidem. (4)

5 WARNINGS AND PRECAUTIONS

- CNS Depressant Effects: Impairs alertness and motor coordination, including risk of morning impairment. Risk increases with dose and use with other CNS depressants and alcohol. Instruct patients on correct use. (5.2)
- Need to Evaluate for Co-morbid Diagnosis: Reevaluate if insomnia persists after 7 to 10 days of use. (5.3)
- Severe Anaphylactic and Anaphylactoid Reactions: angioedema and anaphylaxis have been reported. Do not rechallenge if such reactions occur. (5.4)
- Abnormal Thinking and Behavioral Changes: Changes including decreased inhibition, bizarre behavior, agitation and depersonalization have been reported. Immediately evaluate any new onset behavioral changes. (5.5)
- Depression: Worsening of depression or suicidal thinking may occur. Prescribe the least amount of tablets feasible to avoid intentional overdose. (5.6)
- Respiratory Depression: Consider this risk before prescribing in patients with compromised respiratory function. (5.7)
- Withdrawal Effects: Symptoms may occur with rapid dose reduction or discontinuation. (5.8, 9.3)

6 ADVERSE REACTIONS

Most commonly observed adverse reactions were:

Short term (< 10 nights): Drowsiness, dizziness, and diarrhea
Long term (28-35 nights): Dizziness and drugged feelings (6.1)

To report SUSPECTED ADVERSE REACTIONS, contact Meda Pharmaceuticals Inc. at 1-866-444-7799 or FDA at 1-800-FDA-1088 or www.fda.gov/medwatch.

7 DRUG INTERACTIONS

- CNS-depressants, including alcohol: Possible adverse additive CNS-depressant effects (5.1, 7.1)
- Imipramine: decreased alertness observed (7.1)
- Chlorpromazine: impaired alertness and psychomotor performance observed (7.1)
- Rifampin: combination use may decrease effects (7.2)
- Ketoconazole: combination use may increase effect (7.2)

8 USE IN SPECIFIC POPULATIONS

- Pregnancy: May cause respiratory depression and sedation in neonates with exposure late in third trimester. (8.1)
- Lactation: A lactating woman may pump and discard breast milk during treatment and for 23 hours after Edluar administration. (8.2)
- Pediatric use: Safety and effectiveness not established. Hallucinations (incidence rate 7%) and other psychiatric and/or nervous system adverse reactions were observed frequently in a study of pediatric patients with Attention-Deficit/Hyperactivity Disorder. (5.4, 8.4)

FULL PRESCRIBING INFORMATION

WARNING: COMPLEX SLEEP BEHAVIORS

Complex sleep behaviors including sleep-walking, sleep-driving, and engaging in other activities while not fully awake may occur following use of Edluar. Some of these events may result in serious injuries, including death. Discontinue Edluar immediately if a patient experiences a complex sleep behavior [see Contraindications (4) and Warnings and Precautions (5.1)].

1 INDICATIONS AND USAGE

Edluar (zolpidem tartrate) sublingual tablets are indicated for the short-term treatment of insomnia characterized by difficulties with sleep initiation [see Clinical Studies (14)].

The clinical trials performed with zolpidem tartrate in support of efficacy were 4-5 weeks in duration with the final formal assessments of sleep latency performed at the end of treatment.

2 DOSAGE AND ADMINISTRATION

2.1 Dosage in Adults

Use the lowest effective dose for the patient. The recommended initial dose is 5 mg for women and either 5 or 10 mg for men, taken only once per night immediately before bedtime with at least 7-8 hours remaining before the planned time of awakening. If the 5 mg dose is not effective, the dose can be increased to 10 mg. In some patients, the higher morning blood levels following use of the 10 mg dose increase the risk of next day impairment of driving and other activities that require full alertness [see Warnings and Precautions (5.1)]. The total dose of Edluar should not exceed 10 mg once daily immediately before bedtime.

The recommended initial doses for women and men are different because zolpidem clearance is lower in women.

2.2 Special Populations

Elderly or debilitated patients may be especially sensitive to the effects of zolpidem tartrate. Patients with hepatic insufficiency do not clear the drug as rapidly as normal subjects. The recommended dose of Edluar in both of these patient populations is 5 mg once daily immediately before bedtime [see Warnings and Precautions (5.1); Use in Specific Populations (8.5)].

2.3 Use with CNS Depressants

Dosage adjustment may be necessary when Edluar is combined with other CNS-depressant drugs because of the potentially additive effects [see Warnings and Precautions (5.1)].

2.4 Administration

The effect of Edluar may be slowed by ingestion with or immediately after a meal.

Edluar sublingual tablet should be placed under the tongue, where it will disintegrate. The tablet should not be swallowed and the tablet should not be taken with water.

3 DOSAGE FORMS AND STRENGTHS

Edluar is available in 5 mg and 10 mg strength tablets for sublingual administration. Tablets are not scored.

Edluar 5 mg sublingual tablets are round white, flat-faced, bevel-edged, with debossed V on one side.

Edluar 10 mg sublingual tablets are round white, flat-faced, bevel-edged, with debossed X on one side.

4 CONTRAINDICATIONS

Edluar is contraindicated in patients:

- who have experienced complex sleep behaviors after taking Edluar [see Warnings and Precautions (5.1)].
- with known hypersensitivity to zolpidem. Observed reactions include anaphylaxis and angioedema [see Warnings and Precautions (5.4)].

5 WARNINGS AND PRECAUTIONS

5.1 Complex Sleep Behaviors

Complex sleep behaviors including sleep-walking, sleep-driving, and engaging in other activities while not fully awake may occur following use of zolpidem. Patients can be seriously injured or injure others during complex sleep behaviors. Such injuries may result in a fatal outcome. Other complex sleep behaviors (e.g., preparing and eating food, making phone calls, or having sex) have also been reported. Patients usually do not remember these events. Post-marketing reports have shown that complex sleep behaviors may occur with zolpidem alone at recommended dosages, with or without the concomitant use of alcohol or other central nervous system (CNS) depressants [see Drug Interactions (7.1)]. Discontinue Edluar immediately if a patient experiences a complex sleep behavior.

5.2 CNS Depressant Effects and Next-Day Impairment

Edluar, like other sedative-hypnotic drugs, CNS depressant effects. Co-administration with other CNS depressants (e.g., benzodiazepines, opioids, tricyclic antidepressants, alcohol) increases the risk of CNS depression. Dosage adjustments of Edluar and of other concomitant CNS depressants may be necessary when Edluar is administered with such agents because of the potentially additive effects. The use of Edluar with other sedative-hypnotics (including other zolpidem products) at bedtime or the middle of the night is not recommended [see Dosage and Administration (2.3)].

The risk of next-day psychomotor impairment, including impaired driving, is increased if Edluar is taken with less than a full night of sleep remaining (7 to 8 hours); if a higher than the recommended dose is taken; if co-administered with other CNS depressants; or if co-administered with other drugs that increase the blood level of zolpidem. Patients should be cautioned against driving and other activities requiring complete mental alertness if Edluar is taken in these circumstances.

Because Edluar can cause drowsiness and a decreased level of consciousness, patients, particularly the elderly, are at higher risk of falls.

5.3 Need to Evaluate for Co-morbid Diagnoses

Because sleep disturbances may be the presenting manifestation of a physical and/or psychiatric disorder, symptomatic treatment of insomnia should be initiated only after a careful evaluation of the patient. The failure of insomnia to remit after 7 to 10 days of treatment may indicate the presence of a primary psychiatric and/or medical illness that should be evaluated. Worsening of insomnia or the emergence of new thinking or behavior abnormalities may be the consequence of an unrecognized psychiatric or physical disorder. Such findings have emerged during the course of treatment with sedative/hypnotic drugs, including zolpidem.

5.4 Severe Anaphylactic and Anaphylactoid Reactions

Cases of angioedema involving the tongue, glottis or larynx have been reported in patients after taking the first or subsequent doses of sedative-hypnotics, including zolpidem tartrate. Some patients have had additional symptoms such as dyspnea, throat closing or nausea and vomiting that suggest anaphylaxis. Some patients have required medical therapy in the emergency department. If angioedema involves the throat, glottis or larynx, airway obstruction may occur and be fatal. Patients who develop angioedema after treatment with Edluar should not be rechallenged with the drug.

5.5 Abnormal Thinking and Behavioral Changes

Abnormal thinking and behavior changes have been reported in patients treated with sedative/hypnotics, including zolpidem. Some of these changes included decreased inhibition (e.g. aggressiveness and extroversion that seemed out of character), bizarre behavior, agitation and depersonalization. Visual and auditory hallucinations have been reported.

In controlled trials of zolpidem tartrate 10 mg taken at bedtime, <1% of adults with insomnia who received zolpidem reported hallucinations. In a clinical trial, 7% of pediatric patients treated with zolpidem tartrate 0.25 mg/kg taken at bedtime reported hallucinations, versus 0% treated with placebo [see Use in Specific Populations (8.4)].

It can rarely be determined with certainty whether a particular instance of the abnormal behaviors listed above is drug induced, spontaneous in origin, or a result of an underlying psychiatric or physical disorder. Nonetheless, the emergence of any new behavioral sign or symptom of concern requires careful and immediate evaluation.

5.6 Use in Patients with Depression

In primarily depressed patients treated with sedative-hypnotics, worsening of depression, and suicidal thoughts and actions (including completed suicides), have been reported. Suicidal tendencies may be present in such patients and protective measures may be required. Intentional overdosage is more common in this group of patients; therefore, the least amount of drug that is feasible should be prescribed for the patient at any one time.

5.7 Respiratory Depression

Although studies with 10 mg zolpidem tartrate did not reveal respiratory depressant effects at hypnotic doses in healthy subjects or in patients with mild-to-moderate chronic obstructive pulmonary disease (COPD), a reduction in the Total Arousal Index, together with a reduction in lowest oxygen saturation and increase in the time of oxygen desaturation below 80% and 90%, was observed in patients with mild-to-moderate sleep apnea when treated with zolpidem compared to placebo. Since sedative-hypnotics have the capacity to depress respiratory drive, precautions should be taken if Edluar is prescribed to patients with compromised respiratory function. Post-marketing reports of respiratory insufficiency in patients receiving 10 mg of zolpidem tartrate, most of whom had pre-existing respiratory impairment, have been reported. The risks of respiratory depression should be considered prior to prescribing Edluar in patients with respiratory impairment including sleep apnea and myasthenia gravis.

5.8 Withdrawal Effects

There have been reports of withdrawal signs and symptoms following the rapid dose decrease or abrupt discontinuation of zolpidem. Monitor patients for tolerance, abuse, and dependence [see Drug Abuse and Dependence (9.2) and (9.3)].

6 ADVERSE REACTIONS

The following serious adverse reactions are discussed in greater detail in other sections of the labeling:

- Complex Sleep Behaviors [see Warnings and Precautions (5.1)]
- CNS-Depressant Effects and Next-Day Impairment [see Warnings and Precautions (5.2)]
- Serious Anaphylactic and Anaphylactoid Reactions [see Warning and Precautions (5.4)]
- Abnormal Thinking and Behavioral Changes [see Warning and Precautions (5.5)]
- Withdrawal Effects [see Warning and Precautions (5.8)]

6.1 Clinical Trials Experience

Associated with discontinuation of treatment:

Approximately 4% of 1,701 patients who received zolpidem tartrate at all doses (1.25 to 90 mg) in U.S. premarketing clinical trials discontinued treatment because of an adverse reaction. Reactions most commonly associated with discontinuation from U.S. trials were daytime drowsiness (0.5%), dizziness (0.4%), headache (0.5%), nausea (0.6%), and vomiting (0.5%).

Approximately 4% of 1,959 patients who received zolpidem tartrate at all doses (1 to 50 mg) in similar foreign trials discontinued treatment because of an adverse reaction. Reactions most commonly associated with discontinuation from these trials were daytime drowsiness (1.1%), dizziness/vertigo (0.8%), amnesia (0.5%), nausea (0.5%), headache (0.4%), and falls (0.4%).

Data from a clinical study in which selective serotonin reuptake inhibitor (SSRI)-treated patients were given zolpidem tartrate revealed that four of the seven discontinuations during double-blind treatment with zolpidem (n=95) were associated with impaired concentration, continuing or aggravated depression, and manic reaction; one patient treated with placebo (n=97) was discontinued after an attempted suicide.

Most commonly observed adverse reactions in controlled trials:

During short-term treatment (up to 10 nights) with zolpidem tartrate at doses up to 10 mg, the most commonly observed adverse reactions associated with the use of zolpidem and seen at statistically significant differences from placebo-treated patients were drowsiness (reported by 2% of zolpidem patients), dizziness (1%), and diarrhea (1%). During longer-term treatment (28 to 35 nights) with zolpidem tartrate at doses up to 10 mg, the most commonly observed adverse reactions associated with the use of zolpidem and seen at statistically significant differences from placebo-treated patients were dizziness (5%) and drugged feelings (3%).

Adverse reactions observed at an incidence of ≥1% in controlled trials:

The following tables enumerate treatment-emergent adverse event frequencies that were observed at an incidence equal to 1% or greater among patients with insomnia who received zolpidem tartrate and at a greater incidence than placebo in U.S. placebo-controlled trials. Events reported by investigators were classified utilizing a modified World Health Organization (WHO) dictionary of preferred terms for the purpose of establishing event frequencies. The prescriber should be aware that these figures cannot be used to predict the incidence of side effects in the course of usual medical practice, in which patient characteristics and other factors differ from those that prevailed in these clinical trials. Similarly, the cited frequencies cannot be compared with figures obtained from other clinical investigators involving related drug products and uses, since each group of drug trials is conducted under a different set of conditions. However, the cited figures provide the physician with a basis for estimating the relative contribution of drug and nondrug factors to the incidence of side effects in the population studied.

The following table was derived from a pool of 11 placebo-controlled short-term U.S. efficacy trials involving zolpidem in doses ranging from 1.25 to 20 mg. The table is limited to data from doses up to and including 10 mg, the highest dose recommended for use.

TABLE 1: Incidence of Treatment-Emergent Adverse Experiences in Placebo-Controlled Clinical Trials with zolpidem tartrate lasting up to 10 nights (Percentage of patients reporting)
Body System/ Adverse Event* | Zolipidem tartrate (≤ 10 mg) (N=685) | Placebo (N=473)
Central and Peripheral Nervous System
Headache | 7 | 6
Drowsiness | 2 | -
Dizziness | 1 | -
Gastrointestinal System
Diarrhea | 1 | -
*Reactions reported by at least 1% of patients treated with oral zolpidem and at a greater frequency than placebo.

The following table was derived from a pool of three placebo-controlled long-term efficacy trials involving oral zolpidem. These trials involved patients with chronic insomnia who were treated for 28 to 35 nights with zolpidem at doses of 5, 10, or 15 mg. The table is limited to data from doses up to and including 10 mg, the highest dose recommended for use. The table includes only adverse events occurring at an incidence of at least 1% for zolpidem patients.

TABLE 2: Incidence of Treatment-Emergent Adverse Experiences in Placebo-Controlled Clinical Trials with zolpidem tartrate lasting up to 35 nights (Percentage of patients reporting)
Body System/ Adverse Event* | Zolpidem tartrate (≤ 10 mg) (N=152) | Placebo (N=161)
Autonomic Nervous System | 3 | 1
Dry mouth
Body as a Whole
Allergy | 4 | 1
Back Pain | 3 | 2
Influenza-like symptoms | 2 | -
Chest pain | 1 | -
Cardiovascular System
Palpitation | 2 | -
Central and Peripheral Nervous System
Drowsiness | 8 | 5
Dizziness | 5 | 1
Lethargy | 3 | 1
Drugged feeling | 3 | -
Lightheadedness | 2 | 1
Depression | 2 | 1
Abnormal dreams | 1 | -
Amnesia | 1 | -
Sleep disorder | 1 | -
Gastrointestinal System
Diarrhea | 3 | 2
Abdominal pain | 2 | 2
Constipation | 2 | 1
Respiratory System
Sinusitis | 4 | 2
Pharyngitis | 3 | 1
Skin and Appendages
Rash | 2 | 1
*Reactions reported by at least 1% of patients treated with oral zolpidem and at a greater frequency than placebo.

Dose relationship for adverse reactions associated with oral zolpidem:

There is evidence from dose comparison trials suggesting a dose relationship for many of the adverse reactions associated with oral zolpidem use, particularly for certain CNS and gastrointestinal adverse events.

Oral tissue-related adverse reactions to Edluar:

The effect of chronic daily administration of Edluar on oral tissue was evaluated in a 60-day open-label study in 60 insomniac patients. One patient developed transient sublingual erythema, and another transient paresthesia of the tongue.

Adverse event incidence across the entire preapproval oral zolpidem database:

Zolpidem was administered to 3,660 subjects in clinical trials throughout the U.S., Canada, and Europe. Treatment-emergent adverse events associated with clinical trial participation were recorded by clinical investigators using terminology of their own choosing. To provide a meaningful estimate of the proportion of individuals experiencing treatment-emergent adverse events, similar types of untoward events were grouped into a smaller number of standardized event categories and classified utilizing a modified World Health Organization (WHO) dictionary of preferred terms.

The frequencies presented, therefore, represent the proportions of the 3,660 individuals exposed to zolpidem, at all doses, who experienced an event of the type cited on at least one occasion while receiving zolpidem. All reported treatment-emergent adverse events are included, except those already listed in the table above of adverse events in placebo-controlled studies, those coding terms that are so general as to be uninformative, and those events where a drug cause was remote. It is important to emphasize that, although the events reported did occur during treatment with zolpidem, they were not necessarily caused by it.

Adverse events are further classified within body system categories and enumerated in order of decreasing frequency using the following definitions: frequent adverse events are defined as those occurring in greater than 1/100 subjects; infrequent adverse events are those occurring in 1/100 to 1/1,000 patients; rare events are those occurring in less than 1/1,000 patients.

Autonomic nervous system: Infrequent: increased sweating, pallor, postural hypotension, syncope.
Rare: abnormal accommodation, altered saliva, flushing, glaucoma, hypotension, impotence, increased saliva, tenesmus.

Body as a whole: Frequent: asthenia. Infrequent: edema, falling, fever, malaise, trauma.
Rare: allergic reaction, allergy aggravated, anaphylactic shock, face edema, hot flashes, increased ESR, pain, restless legs, rigors, tolerance increased, weight decrease.

Cardiovascular system: Infrequent: cerebrovascular disorder, hypertension, tachycardia.
Rare: angina pectoris, arrhythmia, arteritis, circulatory failure, extrasystoles, hypertension aggravated, myocardial infarction, phlebitis, pulmonary embolism, pulmonary edema, varicose veins, ventricular tachycardia.

Central and peripheral nervous system: Frequent: ataxia, confusion, euphoria, headache, insomnia, vertigo.
Infrequent: agitation, anxiety, decreased cognition, detached, difficulty concentrating, dysarthria, emotional lability, hallucination, hypoesthesia, illusion, leg cramps, migraine, nervousness, paresthesia, sleeping (after daytime dosing), speech disorder, stupor, tremor.
Rare: abnormal gait, abnormal thinking, aggressive reaction, apathy, appetite increased, decreased libido, delusion, dementia, depersonalization, dysphasia, feeling strange, hypokinesia, hypotonia, hysteria, intoxicated feeling, manic reaction, neuralgia, neuritis, neuropathy, neurosis, panic attacks, paresis, personality disorder, somnambulism, suicide attempts, tetany, yawning.

Gastrointestinal system: Frequent: dyspepsia, hiccup, nausea.
Infrequent: anorexia, constipation, dysphagia, flatulence, gastroenteritis, vomiting.
Rare: enteritis, eructation, esophagospasm, gastritis, hemorrhoids, intestinal obstruction, rectal hemorrhage, tooth caries.

Hematologic and lymphatic system: Rare: anemia, hyperhemoglobinemia, leukopenia, lymphadenopathy, macrocytic anemia, purpura, thrombosis.

Immunologic system: Infrequent: infection.
Rare: abscess herpes simplex herpes zoster, otitis externa, otitis media.

Liver and biliary system: Infrequent: abnormal hepatic function, increased SGPT.
Rare: bilirubinemia, increased SGOT.

Metabolic and nutritional: Infrequent: hyperglycemia, thirst.
Rare: gout, hypercholesterolemia, hyperlipidemia, increased alkaline phosphatase, increased BUN, periorbital edema.

Musculoskeletal system: Frequent: arthralgia, myalgia. Infrequent: arthritis.
Rare: arthrosis, muscle weakness, sciatica, tendinitis.

Reproductive system: Infrequent: menstrual disorder, vaginitis.
Rare: breast fibroadenosis, breast neoplasm, breast pain.

Respiratory system: Frequent: upper respiratory infection. Infrequent: bronchitis, coughing, dyspnea, rhinitis.
Rare: bronchospasm, epistaxis, hypoxia, laryngitis, pneumonia.

Skin and appendages: Infrequent: pruritus.
Rare: acne, bullous eruption, dermatitis, furunculosis, injection-site inflammation, photosensitivity reaction, urticaria.

Special senses: Frequent: diplopia, vision abnormal. Infrequent: eye irritation, eye pain, scleritis, taste perversion, tinnitus.
Rare: conjunctivitis, corneal ulceration, lacrimation abnormal, parosmia, photopsia.

Urogenital system: Frequent: urinary tract infection. Infrequent: cystitis, urinary incontinence.
Rare: acute renal failure, dysuria, micturition frequency, nocturia, polyuria, pyelonephritis, renal pain, urinary retention.

7 DRUG INTERACTIONS

7.1 CNS-active Drugs

CNS Depressants

Co-administration of zolpidem with other CNS depressants increases the risk of CNS depression [see Warnings and Precautions (5.1, 5.2)]. Zolpidem tartrate was evaluated in healthy volunteers in single-dose interaction studies for several CNS drugs.

Imipramine, Chlorpromazine

Imipramine in combination with zolpidem produced no pharmacokinetic interaction other than a 20% decrease in peak levels of imipramine, but there was an additive effect of decreased alertness. Similarly, chlorpromazine in combination with zolpidem produced no pharmacokinetic interaction, but there was an additive effect of decreased alertness and psychomotor performance [see Clinical Pharmacology (12.3)].

Haloperidol

A study involving haloperidol and zolpidem revealed no effect of haloperidol on the pharmacokinetics or pharmacodynamics of zolpidem. The lack of a drug interaction following single-dose administration does not predict the absence of an effect following chronic administration [see Clinical Pharmacology (12.3)].

Alcohol

An additive adverse effect on psychomotor performance between alcohol and oral zolpidem was demonstrated [see Warnings and Precautions (5.1)].

Sertraline

Concomitant administration of zolpidem and sertraline increases exposure to zolpidem and may increase the pharmacodynamics effect of zolpidem [see Clinical Pharmacology (12.3)].

Fluoxetine

After multiple doses of zolpidem tartrate and fluoxetine an increase in the zolpidem half-life (17%) was observed. There was no evidence of an additive effect in psychomotor performance [see Clinical Pharmacology (12.3)].

7.2 Drugs That Affect Drug Metabolism Via Cytochrome P450

Some compounds known to inhibit CYP3A may increase exposure to zolpidem. The effect of other P450 enzymes on the exposure to zolpidem is not known.

Rifampin

Rifampin, a CYP3A4 inducer, significantly reduced the exposure to and the pharmacodynamics effects of zolpidem. Use of Rifampin in combination with zolpidem may decrease the efficacy of zolpidem.

Ketoconazole

Ketoconazole, a potent CYP3A4 inhibitor, increased the pharmacodynamics effects of zolpidem. Consideration should be given to using a lower dose of zolpidem when ketoconazole and zolpidem are given together.

8 USE IN SPECIFIC POPULATIONS

8.1 Pregnancy

Risk Summary

Neonates born to mothers using zolpidem late in the third trimester of pregnancy have been reported to experience symptoms of respiratory depression and sedation (see Clinical Considerations and Data). Published data on the use of zolpidem during pregnancy have not identified a drug-associated risk of and major birth defects (see Data). Oral administration of zolpidem to pregnant rats and rabbits did not indicate a risk for adverse effects on fetal development at clinically relevant doses (see Data).

The estimated background risk of major birth defects and miscarriage for the indicated populations are unknown. All pregnancies have a background risk of birth defect, loss, or other adverse outcomes. In the U.S. general population, the estimated background risk of major birth defects and miscarriage in clinically recognized pregnancies is 2 to 4% and 15 to 20%, respectively.

Clinical Considerations

Fetal/neonatal adverse reactions

Zolpidem crosses the placenta and may produce respiratory depression and sedation in neonates. Monitor neonates exposed to Edluar during pregnancy and labor for signs of excess sedation, hypotonia, and respiratory depression and manage accordingly.

Data

Human Data

Published data from observational studies, birth registries and case reports on the use of zolpidem during pregnancy have not identified a drug-associated risk of major birth defects.

There are limited postmarketing reports of severe to moderate cases of respiratory depression that occurred after birth in neonates whose mothers had taken zolpidem during pregnancy. These cases required artificial ventilation or intra-tracheal intubation. The majority of neonates recovered within hours to a few weeks after birth once treated.

Zolpidem has been shown to cross the placenta.

Animal Data

Oral administration of zolpidem to pregnant rats during the period of organogenesis at 4, 20, and 100 mg base/kg/day, which are approximately 5, 25, and 120 times the MRHD of 10 mg/day (8 mg zolpidem base) based on mg/m^2 body surface area, caused delayed fetal development (incomplete fetal skeletal ossification) at maternally toxic (ataxia) doses 25 and 120 times the MRHD based on mg/m^2 body surface area.

Oral administration of zolpidem to pregnant rabbits during the period of organogenesis at 1, 4, and 16 mg base/kg/day, which are approximately 2.5, 10, and 40 times the MRHD of 10 mg/day (8 mg zolpidem base) based on mg/m^2 body surface area caused embryo-fetal death and delayed fetal development (incomplete fetal skeletal ossification) at a maternally toxic (decreased body weight gain) dose 40 times the MRHD based on mg/m^2 body surface area.

Oral administration of zolpidem to pregnant rats from day 15 of gestation through lactation at 4, 20, and 100 mg base/kg/day, which are approximately 5, 25, and 120 times the MRHD of 10 mg/day (8 mg zolpidem base) based on mg/m^2 body surface area, delayed offspring growth and decreased survival at doses 25 and 120 times, respectively, the MRHD based on mg/m^2 body surface area.

8.2 Lactation

Risk Summary

Limited data from published literature reports the presence of zolpidem in human milk. There are reports of excess sedation in infants exposed to zolpidem through breastmilk (see Clinical Considerations). There is no information on the effects of zolpidem on milk production. The developmental and health benefits of breastfeeding should be considered along with the mother’s clinical need for Edluar and any potential adverse effects on the breastfed infant from Edluar or from the underlying maternal condition.

Clinical Considerations

Infants exposed to Edluar through breastmilk should be monitored for excess sedation, hypotonia, and respiratory depression. A lactating woman may consider interrupting breastfeeding and pumping and discarding breast milk during treatment and for 23 hours (approximately 5 elimination half-lives) after Edluar administration in order to minimize drug exposure to a breast fed infant.

8.4 Pediatric Use

Edluar is not recommended for use in children. Safety and effectiveness in pediatric patients have not been established in pediatric patients below the age of 18.

In an 8-week controlled study in 201 pediatric patients (aged 6-17 years) with insomnia associated with attention-deficit/hyperactivity disorder (ADHD), an oral solution of zolpidem tartrate dosed at 0.25mg/kg at bedtime did not decrease sleep latency compared to placebo. Ten patients on zolpidem (7.4%) discontinued treatment due to an adverse reaction.

Psychiatric and nervous system disorders comprised the most frequent (>5%) treatment emergent adverse reactions observed with zolpidem versus placebo and included dizziness (23.5% vs. 1.5%), headache (12.5% vs. 9.2%), and hallucinations reported in 7% of the pediatric patients who received zolpidem; none of the pediatric patients who received placebo reported hallucinations [see Warnings and Precautions (5.4)].

8.5 Geriatric Use

A total of 154 patients in U.S. controlled clinical trials and 897 patients in non-U.S. clinical trials who received oral zolpidem were ≥60 years of age. For a pool of U.S. patients receiving zolpidem tartrate at doses of ≤10 mg or placebo, there were three adverse events occurring at an incidence of at least 3% for zolpidem and for which the zolpidem incidence was at least twice the placebo incidence (i.e., they could be considered drug-related).

Adverse Event | Zolpidem | Placebo
Dizziness | 3% | 0%
Drowsiness | 5% | 2%
Diarrhea | 3% | 1%

A total of 30/1,959 (1.5%) non-U.S. patients receiving zolpidem tartrate reported falls, including 28/30 (93%) who were ≥70 years of age. Of these 28 patients, 23 (82%) were receiving zolpidem doses >10 mg. A total of 24/1,959 (1.2%) non-U.S. patients receiving zolpidem reported confusion, including 18/24 (75%) who were ≥70 years of age. Of these 18 patients, 14 (78%) were receiving zolpidem doses >10 mg.

The dose of Edluar in elderly patients is 5 mg to minimize adverse effects related to impaired motor and/or cognitive performance and unusual sensitivity to sedative/hypnotic drugs [see Dosage and Administration (2), Warnings and Precautions (5) Clinical Pharmacology (12) and Clinical Studies (14)].

8.6 Gender Difference in Pharmacokinetics

Women clear zolpidem tartrate from the body at a lower rate than men, Cmax and AUC parameters of zolpidem were approximately 45% higher at the same dose in female subjects compared with male subjects. Given the higher blood levels of zolpidem tartrate in women compared to men at a given dose, the recommended dose of Edluar for adult women is 5 mg, and the recommended dose for adult men is 5 or 10 mg.

In geriatric patients, clearance of zolpidem is similar in men and women. The recommended dose of Edluar in geriatric patients is 5 mg regardless of gender.

9 DRUG ABUSE AND DEPENDENCE

9.1 Controlled Substance

Edluar contains the same active substance, zolpidem tartrate, as zolpidem tartrate oral tablets and is classified as a Schedule IV controlled substance by federal regulation.

9.2 Abuse

Abuse and addiction are separate and distinct from physical dependence and tolerance. Abuse is characterized by misuse of the drug for non-medical purposes, often in combination with other psychoactive substances. Tolerance is a state of adaptation in which exposure to a drug induces changes that result in a diminution of one or more of the drug effects over time. Tolerance may occur to both desired and undesired effects of drugs and may develop at different rates for different effects.

Addiction is a primary, chronic, neurobiological disease with genetic, psychosocial, and environmental factors influencing its development and manifestations. It is characterized by behaviors that include one or more of the following: impaired control over drug use, compulsive use, continued use despite harm, and craving. Drug addiction is a treatable disease, using a multidisciplinary approach, but relapse is common.

Studies of abuse potential in former drug abusers found that the effects of single doses of zolpidem tartrate 40 mg were similar, but not identical, to diazepam 20 mg, while zolpidem tartrate 10 mg was difficult to distinguish from placebo.

Because persons with a history of addiction to or abuse of, drugs or alcohol are at increased risk for misuse, abuse, and addiction of Edluar, they should be monitored carefully when receiving Edluar or any other hypnotic.

9.3 Dependence

Physical dependence is a state of adaptation that is manifested by a specific withdrawal syndrome that can be produced by abrupt cessation, rapid dose reduction, decreasing blood level of the drug, and/or administration of an antagonist.

Sedative/hypnotics have produced withdrawal signs and symptoms following abrupt discontinuation. These reported symptoms range from mild dysphoria and insomnia to a withdrawal syndrome that may include abdominal and muscle cramps, vomiting, sweating, tremors, and convulsions. The following adverse events which are considered to meet the DSM-III-R criteria for uncomplicated sedative/hypnotic withdrawal were reported during U.S. clinical trials following placebo substitution occurring within 48 hours following last zolpidem tartrate treatment: fatigue, nausea, flushing, lightheadedness, uncontrolled crying, emesis, stomach cramps, panic attack, nervousness, and abdominal discomfort. These reported adverse events occurred at an incidence of 1% or less. However, available data cannot provide a reliable estimate of the incidence, if any, of dependence during treatment at recommended doses. Post-marketing reports of abuse, dependence and withdrawal have been received.

10 OVERDOSAGE

10.1 Signs and Symptoms

In postmarketing experience of overdose with zolpidem tartrate alone, or in combination with CNS-depressant agents, impairment of consciousness ranging from somnolence to coma, cardiovascular and/or respiratory compromise, and fatal outcomes have been reported.

10.2 Recommended Treatment

Based on data obtained for zolpidem tartrate, general symptomatic and supportive measures for overdose with Edluar should be used along with immediate gastric lavage where appropriate. Intravenous fluids should be administered as needed. Zolpidem’s sedative/hypnotic effect was shown to be reduced by flumazenil and therefore may be useful; however, flumazenil administration may contribute to the appearance of neurological symptoms (convulsions). As in all cases of drug overdose, respiration, pulse, blood pressure, and other appropriate signs should be monitored and general supportive measures employed. Hypotension and CNS depression should be monitored and treated by appropriate medical intervention. Sedating drugs should be withheld following zolpidem overdosage, even if excitation occurs. The value of dialysis in the treatment of overdosage has not been determined, although hemodialysis studies in patients with renal failure receiving therapeutic doses have demonstrated that zolpidem is not dialyzable.

As with the management of all overdosage, the possibility of multiple drug ingestion should be considered. The physician may wish to consider contacting a poison control center for up-to-date information on the management of hypnotic drug product overdosage.

11 DESCRIPTION

Edluar contains zolpidem tartrate, a gamma-aminobutyric acid (GABA) A receptor positive modulator of the imidazopyridine class. Edluar is available in 5 mg and 10 mg strength tablets for sublingual administration.

Chemically, zolpidem tartrate is N,N,6-trimethyl-2-p-tolylimidazo[1,2-a] pyridine-3-acetamide L-(+)-tartrate (2:1). It has the following structure:

Zolpidem tartrate, USP is a white to almost white crystalline powder that is sparingly soluble in water, alcohol, and propylene glycol. It has a molecular weight of 764.88.

Each Edluar tablet includes the following inactive ingredients: mannitol, colloidal silicon dioxide, silicified microcrystalline cellulose, croscarmellose sodium, saccharin sodium, and magnesium stearate.

12 CLINICAL PHARMACOLOGY

12.1 Mechanism of Action

Zolpidem is a GABA A receptor positive modulator presumed to exert its therapeutic effects in the short-term treatment of insomnia through binding to the benzodiazepine site of α1 subunit containing GABA A receptors, increasing the frequency of chloride channel opening resulting in the inhibition of neuronal excitation.

12.2 Pharmacodynamics

Zolpidem binds to GABAA receptors with a greater affinity for α1 subunit relative to α2 and α3 subunit containing receptors. Zolpidem has no appreciable binding affinity for α5 subunit containing GABAA receptors. This binding profile may explain the relative absence of myorelaxant effects in animal studies. Zolpidem has no appreciable binding affinity for dopaminergic D2, serotonergic 5HT2, adrenergic, histaminergic or muscarinic receptors.

12.3 Pharmacokinetics

Absorption:

Edluar (zolpidem tartrate) sublingual tablets are bioequivalent to Ambien® tablets (Sanofi-Aventis) with respect to Cmax and AUC. Similar to zolpidem tartrate oral tablets, Edluar sublingual tablets result in a pharmacokinetic profile characterized by rapid absorption.

Following administration of single 10 mg Edluar, in 18 healthy adult subjects (18-65 years of age), the mean peak concentration (Cmax) of zolpidem was 106 ng/mL (range: 52 to 205 ng/ml) occurring at a median time (Tmax) of 82 minutes (range: 30-180 min).

A food-effect study in 18 healthy volunteers compared the pharmacokinetics of Edluar 10 mg when administered while fasting or within 20 minutes after a high fat meal. The mean AUC and Cmax were decreased by 20% and 31%, respectively, while median Tmax was prolonged by 28% (from 82 to 105 min). The half-life remained unchanged. These results suggest that, for faster sleep onset, Edluar should not be administered with or immediately after a meal.

Distribution:

Based on data obtained with oral zolpidem, the total protein binding was found to be 92.5 ± 0.1% and remained constant, independent of concentration between 40 and 790 ng/mL.

Metabolism:

Based on data obtained with oral zolpidem, zolpidem is converted to inactive metabolites that are eliminated primarily by renal excretion.

Elimination:

When Edluar administered as a single 5 or 10 mg dose in healthy adult subjects, the mean zolpidem elimination half-life was 2.85 hours (range: 1.57-6.73 hr) and 2.65 hours (range: 1.75 to 3.77 hr) respectively.

Special Populations

Elderly:

In the elderly, the dose for Edluar should be 5 mg [see Warnings and Precautions (5) and Dosage and Administration (2)]. This recommendation is based on several studies with zolpidem tartrate in which the mean Cmax, T1/2, and AUC were significantly increased when compared to results in young adults. In one study of eight elderly subjects (>70 years), the means for Cmax, T1/2, and AUC significantly increased by 50% (255 vs. 384 ng/mL), 32% (2.2 vs. 2.9 hr), and 64% (955 vs. 1,562 ng•hr/mL), respectively, as compared to younger adults (20 to 40 years) following a single 20 mg oral dose. Zolpidem did not accumulate in elderly subjects following nightly oral dosing of 10 mg for 1 week.

Hepatic Impairment:

The pharmacokinetics of zolpidem tartrate in eight patients with chronic hepatic insufficiency were compared to results in healthy subjects. Following a single 20-mg oral zolpidem tartrate dose, mean Cmax and AUC were found to be two times (250 vs. 499 ng/mL) and five times (788 vs. 4,203 ng•hr/mL) higher, respectively, in hepatically-compromised patients. Tmax did not change. The mean half-life in cirrhotic patients of 9.9 hr (range: 4.1 to 25.8 hr) was greater than that observed in normals of 2.2 hr (range: 1.6 to 2.4 hr). Dosing with Edluar should be modified accordingly in patients with hepatic insufficiency [see Dosage and Administration (2.2)].

Renal Impairment:

The pharmacokinetics of zolpidem tartrate were studied in 11 patients with end-stage 4 renal failure (mean ClCr = 6.5 ± 1.5 mL/min) undergoing hemodialysis three times a week, who were dosed with zolpidem tartrate 10 mg orally each day for 14 or 21 days. No statistically significant differences were observed for Cmax, Tmax, half-life, and AUC between the first and last day of drug administration when baseline concentration adjustments were made. Zolpidem was not hemodialyzable. No accumulation of unchanged drug appeared after 14 or 21 days. Zolpidem pharmacokinetics were not significantly different in renally-impaired patients. No dosage adjustment is necessary in patients with compromised renal function.

Drug Interactions

CNS-depressants:

Co-administration of zolpidem with other CNS depressants increases the risk of CNS depression [see Warnings and Precautions (5.1)]. Zolpidem tartrate was evaluated in healthy volunteers in single-dose interaction studies for several CNS drugs. Imipramine in combination with zolpidem produced no pharmacokinetic interaction other than a 20% decrease in peak levels of imipramine, but there was an additive effect of decreased alertness. Similarly, chlorpromazine in combination with zolpidem produced no pharmacokinetic interaction, but there was an additive effect of decreased alertness and psychomotor performance.

A study involving haloperidol and zolpidem revealed no effect of haloperidol on the pharmacokinetics or pharmacodynamics of zolpidem. The lack of a drug interaction following single-dose administration does not predict the absence of an effect following chronic administration.

An additive adverse effect on psychomotor performance between alcohol and oral zolpidem was demonstrated [see Warnings and Precautions (5.1)].

Following five consecutive nightly doses at bedtime of oral zolpidem tartrate 10 mg in the presence of sertraline 50 mg (17 consecutive daily doses, at 7:00 am, in healthy female volunteers), zolpidem Cmax was significantly higher (43%) and Tmax was significantly decreased (-53%). Pharmacokinetics of sertraline and N-desmethylsertraline were unaffected by zolpidem.

A single-dose interaction study with zolpidem tartrate 10 mg and fluoxetine 20 mg at steady-state levels in male volunteers did not demonstrate any clinically significant pharmacokinetic or pharmacodynamics interactions. When multiple doses of zolpidem and fluoxetine were given at steady-state and the concentrations evaluated in healthy females, an increase in the zolpidem half-life (17%) was observed. There was no evidence of an additive effect in psychomotor performance.

Drugs that Affect Drug metabolism via Cytochrome P450

Some compounds known to inhibit CYP3A may increase exposure to zolpidem. The effect of inhibitors of other P450 enzymes on the pharmacokinetics of zolpidem is unknown.

A single-dose interaction study with zolpidem tartrate 10 mg and itraconazole 200 mg at steady-state levels in male volunteers resulted in a 34% increase in AUC0-∞ of zolpidem tartrate. There were no pharmacodynamics effects of zolpidem detected on subjective drowsiness, postural sway, or psychomotor performance.

A single-dose interaction study with zolpidem tartrate 10 mg and rifampin 600 mg at steady-state levels in female subjects showed significant reductions of the AUC (-73%), Cmax (-58%), and T½ (-36 %) of zolpidem together with significant reductions in the pharmacodynamics effects of zolpidem tartrate. Rifampin, a CYP3A4 inducer, significantly reduced the exposure to and the pharmacodynamics effects of zolpidem.

A single-dose interaction study with zolpidem 5 mg and ketoconazole, a potent CYP3A4 inhibitor, given as 200 mg twice daily for 2 days increased Cmax of zolpidem (30%) and the total AUC of zolpidem (70%) compared to zolpidem alone and prolonged the elimination half-life (30%) along with an increase in the pharmacodynamics effects of zolpidem. Consideration should be given to using a lower dose of zolpidem when ketoconazole and zolpidem are given together.

Other Drugs with No Interactions with Zolpidem

A study involving cimetidine/zolpidem tartrate and ranitidine/zolpidem tartrate combinations revealed no effect of either drug on the pharmacokinetics or pharmacodynamics of zolpidem.

Zolpidem tartrate had no effect on digoxin pharmacokinetics and did not affect prothrombin time when given with warfarin in healthy subjects.

13 NONCLINICAL TOXICOLOGY

13.1 Carcinogenesis, Mutagenesis, Impairment of Fertility

Carcinogenesis:

Zolpidem was administered to mice and rats for 2 years at oral doses of 4, 18, and 80 mg base/kg/day. In mice, these doses are approximately 2.5, 10, and 50 times the maximum recommended human dose (MRHD) of 10 mg/day (8 mg zolpidem base) based on mg/m^2 body surface area and in rats, these doses are approximately 5, 20, and 100 times the MRHD based on mg/m^2 body surface area. No evidence of carcinogenic potential was observed in mice. In rats, renal tumors (lipoma, liposarcoma) were seen at the mid and high doses.

Mutagenesis:

Zolpidem was negative in in vitro (bacterial reverse mutation, mouse lymphoma, and chromosomal aberration) and in vivo (mouse micronucleus) genetic toxicology assays.

Impairment of Fertility:

Zolpidem was administered to rats at 4, 20, and 100 mg base/kg/day, which are approximately 5, 25, and 120 times the maximum recommended human dose (MRHD) of 10 mg/day (8 mg zolpidem base) based on mg/m^2 body surface area, prior to and during mating, and continuing in females through postpartum day 25. Zolpidem caused irregular estrus cycles and prolonged precoital intervals at the highest dose tested, which is approximately 120 times the MRHD based on mg/m^2 body surface area. The NOAEL for these effects is 25 times the MRHD based on a mg/m^2 body surface area. There was no impairment of fertility at any dose tested.

14 CLINICAL STUDIES

14.1 Transient Insomnia

Normal adults experiencing transient insomnia (n = 462) during the first night in a sleep laboratory were evaluated in a double-blind, parallel group, single night trial comparing two doses of zolpidem tartrate oral tablets (7.5 and 10 mg) and placebo. Both zolpidem doses were superior to placebo on objective (polysomnographic) measures of sleep latency, sleep duration, and number of awakenings.

Normal elderly adults (mean age 68) experiencing transient insomnia (n = 35) during the first two nights in a sleep laboratory were evaluated in a double-blind, crossover, 2-night trial comparing four doses of zolpidem (5, 10, 15, and 20 mg) and placebo. All zolpidem doses were superior to placebo on the two primary PSG parameters (sleep latency and efficiency) and all four subjective outcome measures (sleep duration, sleep latency, number of awakenings, and sleep quality).

14.2 Chronic Insomnia

Zolpidem was evaluated in two controlled studies for the treatment of patients with chronic insomnia (most closely resembling primary insomnia, as defined in the APA Diagnostic and Statistical Manual of Mental Disorders, DSM-IV™). Adult outpatients with chronic insomnia (n = 75) were evaluated in a double-blind, parallel group, 5-week trial comparing two doses of zolpidem tartrate and placebo. On objective (polysomnographic) measures of sleep latency and sleep efficiency, zolpidem 10 mg was superior to placebo on sleep latency for the first 4 weeks and on sleep efficiency for weeks 2 and 4. Zolpidem was comparable to placebo on number of awakenings at both doses studied.

Adult outpatients (n=141) with chronic insomnia were also evaluated, in a double-blind, parallel group, 4-week trial comparing two doses of zolpidem and placebo. Zolpidem 10 mg was superior to placebo on a subjective measure of sleep latency for all 4 weeks, and on subjective measures of total sleep time, number of awakenings, and sleep quality for the first treatment week.

Increased wakefulness during the last third of the night as measured by polysomnography has not been observed in clinical trials with zolpidem tartrate.

14.3 Studies Pertinent to Safety Concerns for Sedative/Hypnotic Drugs

Next-day residual effects of zolpidem tartrate were evaluated in seven studies involving normal subjects. In three studies in adults (including one study in a phase advance model of transient insomnia) and in one study in elderly subjects, a small but statistically significant decrease in performance was observed in the Digit Symbol Substitution Test (DSST) when compared to placebo. Studies of zolpidem tartrate in non-elderly patients with insomnia did not detect evidence of next-day residual effects using the DSST, the Multiple Sleep Latency Test (MSLT), and patient ratings of alertness.

Rebound effects:

There was no objective (polysomnographic) evidence of rebound insomnia at recommended doses seen in studies evaluating sleep on the nights following discontinuation of zolpidem tartrate. There was subjective evidence of impaired sleep in the elderly on the first post-treatment night at doses of zolpidem tartrate above the recommended elderly dose of 5 mg.

Memory impairment:

Controlled studies in adults utilizing objective measures of memory yielded no consistent evidence of next-day memory impairment following the administration of zolpidem tartrate. However, in one study involving zolpidem doses of 10 and 20 mg, there was a significant decrease in next-morning recall of information presented to subjects during peak drug effect (90 minutes post-dose), i.e., these subjects experienced anterograde amnesia. There was also subjective evidence from adverse event data for anterograde amnesia occurring in association with the administration of zolpidem tartrate, predominantly at doses above 10 mg.

Effects on sleep stages:

In studies that measured the percentage of sleep time spent in each sleep stage, zolpidem tartrate has generally been shown to preserve sleep stages. Sleep time spent in stages 3 and 4 (deep sleep) was found comparable to placebo with only inconsistent, minor changes in REM (paradoxical) sleep at the recommended dose.

16 HOW SUPPLIED/STORAGE AND HANDLING

Edluar is supplied as sublingual tablets in two dosage strengths: Tablets are not scored.

Edluar 5 mg sublingual tablets are round white tablets, flat-faced, bevel-edged with debossed V on one side and supplied as:

NDC Number Size
0037-6050-30 carton of 30 tablets (3 x 10 tablets)

0037-6050-93 carton of 30 tablets (5 x 6 tablets)

The blister packs consist of aluminum/aluminum Child Resistant Control (CRC) blisters.

Edluar 10 mg sublingual tablets are round white tablets, flat-faced, bevel-edged with debossed X on one side and supplied as:

NDC Number Size
0037-6010-30 carton of 30 tablets (3 x 10 tablets)

0037-6010-93 carton of 30 tablets (5 x 6 tablets)

The blister packs consist of aluminum/aluminum Child Resistant Control (CRC) blisters.

Store at controlled room temperature 20-25°C (68-77°F). Protect from light and moisture.

17 PATIENT COUNSELING INFORMATION

See FDA-approved patient labeling (Medication Guide).

Inform patients and their families about the benefits and risks of treatment with Edluar. Inform patients of the availability of a Medication Guide and instruct them to read the Medication Guide prior to initiating treatment with Edluar and with each prescription refill. Review the Edluar Medication Guide with every patient prior to initiation of treatment. Instruct patients or caregivers that Edluar should be taken only as prescribed.

Complex Sleep Behaviors

Instruct patients and their families that Edluar may cause complex sleep behaviors, including sleep-walking, sleep-driving, preparing and eating food, making phone calls, or having sex while not being fully awake. Serious injuries and death have occurred during complex sleep behavior episodes. Tell patients to discontinue Edluar and notify their healthcare provider immediately if they develop any of these symptoms [see Boxed Warning, Warnings and Precautions (5.1)].

CNS-depressant Effects and Next-Day Impairment

Tell patients that Edluar has the potential to cause next-day impairment, and that this risk is increased if dosing instructions are not carefully followed. Tell patients to wait for at least 8 hours after dosing before driving or engaging in other activities requiring full mental alertness. Inform patients that impairment can be present despite feeling fully awake. Advise patients that increased drowsiness and decreased consciousness may increase the risk of falls in some patients [see Warnings and Precautions (5.2)].

Severe Anaphylactic and Anaphylactoid Reactions

Inform patients that severe anaphylactic and anaphylactoid reactions have occurred with zolpidem. Describe the signs/symptoms of these reactions and advise patients to seek medical attention immediately if any of them occur [see Warnings and Precautions (5.4)].

Suicide

Tell patients to immediately report any suicidal thoughts.

Alcohol and Other Drugs

Ask patients about alcohol consumption, medicines they are taking, and drugs they may be taking without a prescription. Advise patients not to use Edluar if they drank alcohol that evening or before bed.

Tolerance, Abuse, and Dependence

Tell patients not to increase the dose of Edluar on their own, and to inform you if they believe the drug “does not work”.

Pregnancy

Advise patients to notify their healthcare provider if they become pregnant or intend to become pregnant during treatment with Edluar. Advise patients that use of Edluar late in the third trimester may cause respiratory depression and sedation in neonates. Advise mothers who used Edluar during the late third trimester of pregnancy to monitor neonates for signs of sleepiness (more than usual), breathing difficulties, or limpness [see Use in Specific Populations (8.1)].

Lactation

Advise breastfeeding mothers using Edluar to monitor infants for increased sleepiness, breathing difficulties, or limpness. Instruct nursing mothers to seek immediate medical care if they notice these signs. A lactating woman may consider pumping and discarding breastmilk during treatment and for 23 hours after Edluar administration to minimize drug exposure to a breastfed infant [see Use in Specific Populations (8.2)].

Administration Instructions

Patients should be counseled to take Edluar right before they get into bed and only when they are able to stay in bed a full night (7-8 hours) before being active again. Edluar tablets should not be taken with or immediately after a meal. Advise patients NOT to take Edluar when drinking alcohol that evening or before bed. Edluar sublingual tablet should be placed under the tongue, where it will disintegrate. The tablet should not be swallowed and the tablet should not be taken with water.

Medication Guide
Edluar® [ED’ – loo-ahr]
(zolpidem tartrate)
sublingual tablets C-IV

Read this Medication Guide that comes with Edluar before you start taking it and each time you get a refill. There may be new information. This Medication Guide does not take the place of talking to your healthcare provider about your medical condition or treatment.

What is the most important information I should know about Edluar?

- Do not take more Edluar than prescribed.
- Do not take Edluar unless you are able to stay in bed a full night (7 to 8 hours) before you must be active again.
- Take Edluar right before you get in bed, not sooner.

Edluar may cause serious side effects, including:

- Complex sleep behaviors that have caused serious injury and death. After taking Edluar, you may get up out of bed while not being fully awake and do an activity that you do not know you are doing (complex sleep behaviors). The next morning, you may not remember that you did anything during the night. These activities may occur with Edluar whether or not you drink alcohol or take other medicines that make you sleepy.
  Reported activities include:
  - driving a car (“sleep-driving”)
  - making and eating food
  - talking on the phone
  - having sex
  - sleep-walking

Stop taking Edluar and call your healthcare provider right away if you find out that you have done any of the above activities after taking Edluar.

Do not take Edluar if you:

- have ever experienced a complex sleep behavior (such as driving a car, making or eating food, talking on the phone, or having sex) while not being fully awake after taking Edluar
- drank alcohol that evening or before bed
- took another medicine to help you sleep

What is Edluar?

Edluar is a sedative-hypnotic (sleep) medicine. Edluar is used in adults for the short-term treatment of a sleep problem called insomnia (trouble falling asleep).

It is not known if Edluar is safe and effective in children under the age of 18 years.

Edluar is a class four (C-IV) federally controlled substance because it can be abused or lead to dependence. Keep Edluar in a safe place to prevent misuse and abuse. Selling or giving away Edluar may harm others, and is against the law. Tell your doctor if you have ever abused or been dependent on alcohol, prescription medicines or street drugs.

Who should not take Edluar?

- Do not take Edluar if you are allergic to zolpidem or any other ingredients in Edluar. See the end of this Medication Guide for a complete list of ingredients in Edluar.
- Do not take Edluar if you have had an allergic reaction to drugs containing zolpidem, such as Ambien, Ambien CR, Zolpimist, or Intermezzo.

Symptoms of a serious allergic reaction to zolpidem can include:

- swelling of your face, lips, and throat that may cause difficulty breathing or swallowing
- nausea and vomiting

What should I tell my healthcare provider before taking Edluar?

Edluar may not be right for you. Before starting Edluar, tell your healthcare provider about all of your health conditions, including if you:

- have a history of depression, mental illness or, suicidal thoughts
- have a history of drug or alcohol abuse or addiction
- have kidney or liver disease
- have lung disease or breathing problems
- are pregnant or planning to become pregnant. Talk to your healthcare provider about the risk to your unborn baby if you take Edluar.
- using Edluar in the last trimester of pregnancy may cause breathing difficulties or excess sleepiness in your newborn. Monitor for signs of sleepiness (more than usual), trouble breathing, or limpness in the newborn if Edluar is taken late in pregnancy.
- are breastfeeding or plan to breastfeed. Edluar passes into your breast milk. Talk to your healthcare provider about the best way to feed your baby while you take Edluar.

Tell your healthcare provider about all of the medicines you take, including prescription and nonprescription medicines, vitamins and herbal supplements.

Medicines can interact with each other, sometimes causing serious side effects.

Do not take Edluar with other medicines that can make you sleepy, unless directed by your healthcare provider.

Know the medicines you take. Keep a list of your medicines with you to show your healthcare provider and pharmacist each time you get a new medicine.

How should I take Edluar?

- See “What is the most important information I should know about Edluar?”
- Take Edluar exactly as prescribed. Only take 1 Edluar tablet a night and only if needed.
- Do not take Edluar if you drank alcohol that evening or before bed.
- You should not take Edluar with or right after a meal. Edluar may help you fall asleep faster if you take it on an empty stomach.
- Do not use the tablet if the seal on the childproof blister pack is broken, or if the blister holding the tablet is broken.
- To open the blister pack, separate the individual blisters at the perforations. Peel off the top layer of paper, and push the tablet through the foil. Alternatively, use scissors to open the blister.
- Place the tablet under the tongue, where it will disintegrate. Do not swallow or take with water.
- Call your healthcare provider if your insomnia worsens or is not better within 7 to 10 days. This may mean that there is another condition causing your sleep problem.
- If you take too much Edluar or overdose, get emergency treatment.

What are the possible side effects of Edluar?

Edluar may cause serious side effects, including:

- getting out of bed while not being fully awake and doing an activity that you do not know you are doing. See “What is the most important information I should know about Edluar?”
- abnormal thoughts and behavior. Symptoms include more outgoing or aggressive behavior than normal, confusion, agitation, hallucinations, worsening of depression, suicidal thoughts or actions.
- memory loss
- anxiety
- severe allergic reactions. Symptoms include swelling of the tongue or throat, trouble breathing. Get emergency medical help if you get these symptoms after taking Edluar.

Call your healthcare provider right away if you have any of the above side effects or any other side effects that worry you while using Edluar.

The most common side effects of Edluar are:

- drowsiness
- dizziness
- diarrhea
- grogginess or feeling as if you have been drugged
- fatigue
- headache

You may still feel drowsy the next day after taking Edluar.

After you stop taking a sleep medicine, you may have symptoms for 1 to 2 days such as:

- trouble sleeping
- nausea
- flushing
- lightheadedness
- uncontrolled crying
- vomiting
- stomach cramps
- panic attack
- nervousness
- stomach area pain

These are not all the side effects of Edluar. Ask your doctor or pharmacist for more information.

Call your healthcare provider for medical advice about side effects. You may report side effects to FDA at 1-800-FDA-1088.

How should I store Edluar?

- Store Edluar at room temperature, between 68°F and 77°F (20° to 25°C).
- Protect from light and moisture.

Keep Edluar and all medicines out of reach of children.

General information about the safe and effective use of Edluar

Medicines are sometimes prescribed for purposes other than those listed in a Medication Guide.

Do not use Edluar for a condition for which it was not prescribed.

Do not share Edluar with other people, even if you think they have the same symptoms that you have. It may harm them and it is against the law.

This Medication Guide summarizes the most important information about Edluar.

If you would like more information, talk with your healthcare provider. You can ask your healthcare provider or pharmacist for information about Edluar that is written for healthcare professionals.

For more information about Edluar, call Meda Pharmaceuticals Inc. at 1-866-444-7799.

What are the ingredients in Edluar?

Active Ingredient: zolpidem tartrate

Inactive Ingredients: mannitol, colloidal silicon dioxide, silicified microcrystalline cellulose, croscarmellose sodium, saccharin sodium, and magnesium stearate.

This Medication Guide has been approved by U.S. Food and Drug Administration.

Manufactured by:
Mylan Laboratories Limited
Hyderabad – 500 096, India

Manufactured for:
Meda Pharmaceuticals Inc.
Somerset, NJ 08873-4120

© 2022 Viatris Inc.
U.S. Patents 9,265,720; 9,597,281

EDLUAR is a registered trademark of Meda Pharmaceuticals Inc., a Viatris company.

The brands listed are trademarks of their respective owners.

MX-IG-6010-03 Rev. 8/2022 75092793

PRINCIPAL DISPLAY PANEL – 5 mg

Rx Only NDC 0037-6050-93

EDLUAR® 5 mg CIV
Zolpidem Tartrate Sublingual Tablets

Each sublingual tablet (to be placed under the tongue) contains 5 mg of zolpidem tartrate, USP. See prescribing information for dosage information.

30 Sublingual Tablets

PHARMACIST:
Dispense the
accompanying
Medication Guide
to each patient.

Store at controlled room temperature 20-25ºC (68-77ºF).
Protect from light and moisture.
Do not use if blisters are torn, or seal is broken.

MX-UC-605093-02

Manufactured for:
Meda Pharmaceuticals Inc.
Somerset, New Jersey 08873-4120

U.S. Patents 9,265,720; 9,597,281

EDLUAR is a registered trademark of
Meda Pharmaceuticals Inc., a Viatris Company.

Made in India

CODE No.: MH/DRUGS/25/NKD/89

PRINCIPAL DISPLAY PANEL – 10 mg

Rx Only NDC 0037-6010-93

EDLUAR® 10 mg CIV
Zolpidem Tartrate Sublingual Tablets

Each sublingual tablet (to be placed under the tongue) contains 10 mg of zolpidem tartrate, USP. See prescribing information for dosage information.

30 Sublingual Tablets

Store at controlled room temperature 20-25ºC (68-77ºF).
Protect from light and moisture.
Do not use if blisters are torn, or seal is broken.

MX-UC-601093-02

Manufactured for:
Meda Pharmaceuticals Inc.
Somerset, New Jersey 08873-4120

U.S. Patents 9,265,720; 9,597,281

EDLUAR is a registered trademark of
Meda Pharmaceuticals Inc., a Viatris Company.

Made in India

CODE No.: MH/DRUGS/25/NKD/89